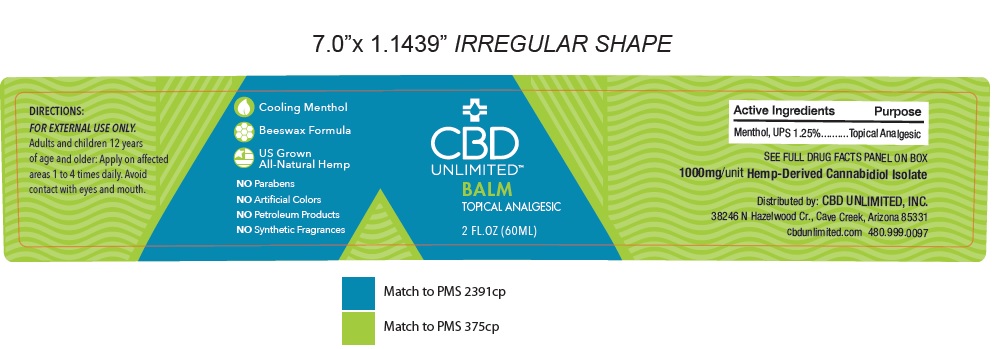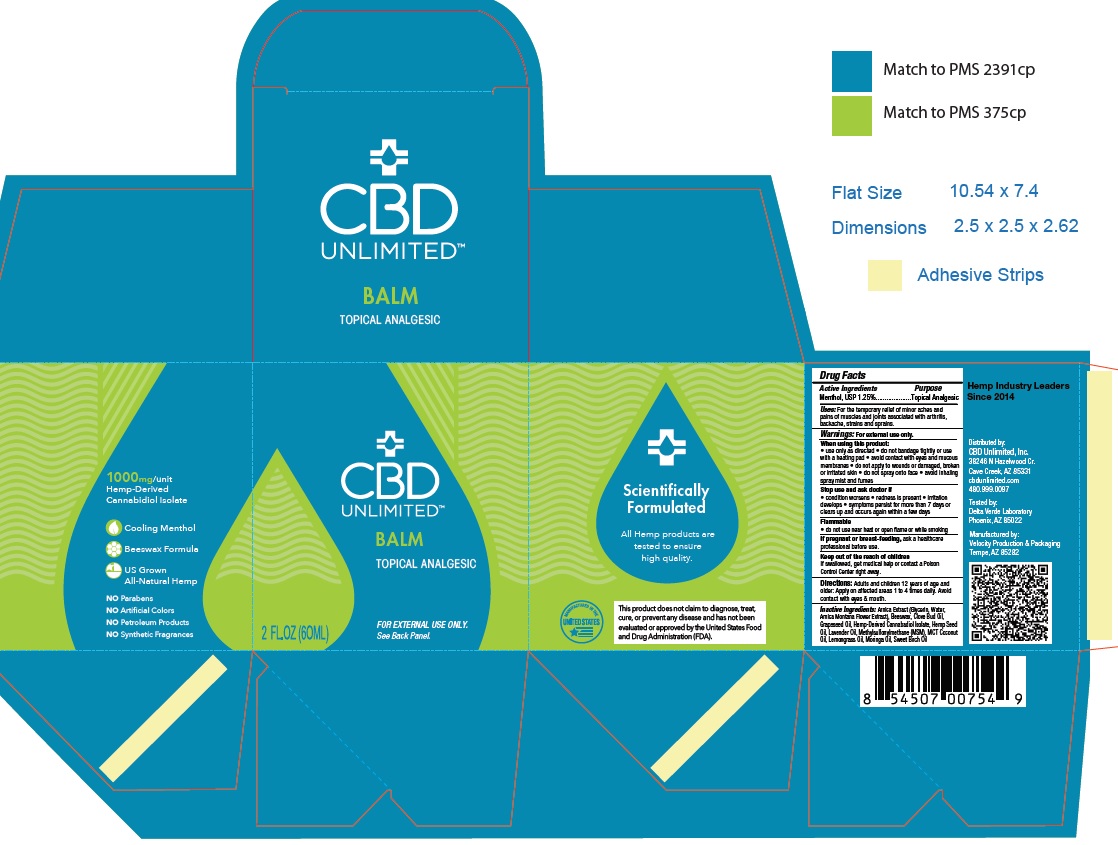 DRUG LABEL: CBD UNLIMITED BALM TOPICAL ANALGESIC
NDC: 73045-003 | Form: CREAM
Manufacturer: ENDEXX CORPORATION
Category: otc | Type: HUMAN OTC DRUG LABEL
Date: 20200505

ACTIVE INGREDIENTS: MENTHOL 125 mg/1 mL
INACTIVE INGREDIENTS: MEDIUM-CHAIN TRIGLYCERIDES; YELLOW WAX; CANNABIDIOL; OLIVE OIL; HETEROTHECA INULOIDES FLOWER; MORINGA OLEIFERA SEED OIL; GRAPE SEED OIL; Cannabis Sativa Seed Oil; Clove Oil; Lavender Oil; East Indian Lemongrass Oil; Methyl Salicylate; Dimethyl Sulfone

CBD UNLIMITED TOPICAL ANALGESIC BALM

Active ingredient

Menthol 1.25%

Purpose

Topical Analgesic

Uses

For the temporary relief of minor aches and
pains of muscles and joints associated with arthritis, backache, strains and sprains.

Warnings:

Warnings: For external use only.

When using this product:
• use only as directed

• do not bandage tightly or use with a heating pad

• avoid contact with eyes and mucous membranes

• do not apply to wounds or damaged, broken or irritated skin

• do not spray onto face

• avoid inhaling spray mist and fumes

Stop use and ask doctor if

• condition worsens

• redness is present

• irritation develops

• symptoms persist for more than 7 days or clears up and occurs again within a few days

Flammable

• do not use near heat or open _ame or while smoking

If pregnant or breast-feeding, ask a healthcare

professional before use.

Keep out of the reach of children

Keep Out of Reach of Children

If swallowed, get medical help or contact a Poison Control Center right away

Directions:

Adults and children 12 years of age and older: Apply on affected areas 1 to 4 times daily.

Avoid contact with eyes & mouth.

Inactive Ingredients

Arnica Extract (Glycerin, Water, Arnica Montana Flower Extract), Beeswax, Clove Bud Oil, Grapeseed Oil, Hemp-Derived Cannabadiol Isolate, Hemp Seed Oil, Lavender Oil, Methylsulfonylmethane (MSM), MCT Coconut Oil, Lemongrass Oil, Moringa Oil, Sweet Birch Oil